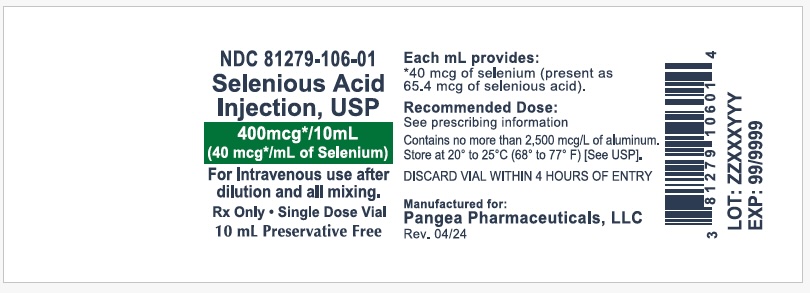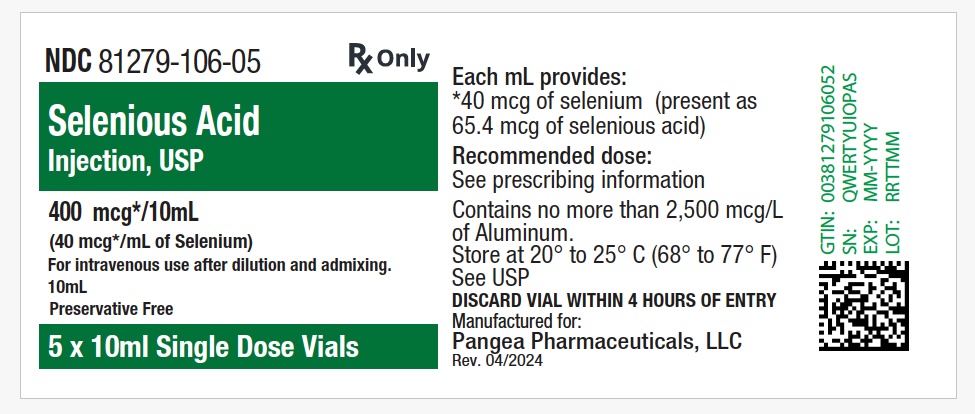 DRUG LABEL: Selenious Acid
NDC: 81279-106 | Form: INJECTION, SOLUTION
Manufacturer: Pangea Pharmaceuticals, LLC
Category: prescription | Type: HUMAN PRESCRIPTION DRUG LABEL
Date: 20260107

ACTIVE INGREDIENTS: SELENIUM 40 ug/1 mL
INACTIVE INGREDIENTS: WATER; NITRIC ACID

SELENIUM INJECTION
Rx Only
TRACE ELEMENT ADDITIVE FOR IV USE AFTER DILUTION

DESCRIPTION

Selenium Injection is a sterile, nonpyrogenic solution for use as an additive to solutions for Total Parenteral Nutrition (TPN). Each mL contains Selenious Acid 65.4 mcg (equivalent to elemental selenium 40 mcg/mL) and Water for Injection q.s. pH may be adjusted with nitric acid to 1.8 to 2.4.

CLINICAL PHARMACOLOGY

Selenium is part of glutathione peroxidase which protects cell components from oxidative damage due to peroxides produced in cellular metabolism.

Prolonged TPN support in humans has resulted in selenium deficiency symptoms which include muscle pain and tenderness. The symptoms have been reported to respond to supplementation of TPN solutions with selenium.

Pediatric conditions, Keshan disease, and Kwashiorkor, have been associated with low dietary intake of selenium. The conditions are endemic to geographical areas with low selenium soil content. Dietary supplementation with selenium salts has been reported to reduce the incidence of the conditions among affected children.

Normal blood levels of selenium in different human populations have been found to vary and depend on the selenium content of the food consumed. Results of surveys carried out in some countries are tabulated below:

Country | Number of Samples | SELENIUM (mcg/100mL) (a)
Country | Number of Samples | Whole Blood | Blood Cells | Plasma / Serum
Canada | 254 Adults | (37.9 ± 7.8) | (23.6 ± 6.0) | (14.4 ± 2.9)
England | 8 (b) | 26 - 37 (32) | - | -
Guatemala & Southern USA | 10 Adults 9 Children (c) | 19 - 28 (22) (23 ± 5) | - (36 ± 12) | - (15 ± 5)
New Zealand (d) | 113 Adults | (5.4 ± 0.1) | (6.6 ± 0.3) | (4.3 ± 0.1)
Thailand | 3 Adults 9 Children (e) | 14.4 - 20.2 (12.0 ± 3.6) (f) | 17.8 - 35.8 (19.5 ± 8.2) | 8.1 - 12.5 (8.3 ± 2.2)
USA | 210 Adults | 15.7 - 25.6 (20.6) | - | -

(a) Mean values with or without standard deviation in parentheses, all other ranges.
(b) Age group unknown.
(c) Three children recovered from Kwashiorkor and the other six under treatment for other diseases.
(d) Low selenium-content soil area.
(e) Well nourished children, three recovered from Kwashiorkor and the other six under treatment for other diseases.
(f) Mean values from seven subjects.

Plasma selenium levels of 0.3 and 0.9 mcg/100 mL have been reported to produce deficiency symptoms in humans.

Selenium is eliminated primarily in urine. However, significant endogenous losses through feces also occur. The rate of excretion and the relative importance of two routes varies with the chemical form of selenium used in supplementation. Ancillary routes of elimination are lungs and skin.

INDICATIONS AND USAGE

Selenium Injection is indicated for use as a supplement to intravenous solutions given for total parenteral nutrition (TPN). Administration of selenium in TPN solutions helps to maintain plasma selenium levels and to prevent depletion of endogenous stores and subsequent deficiency symptoms.

CONTRAINDICATIONS

Selenium Injection should not be given undiluted by direct injection into a peripheral vein because of the potential for infusion phlebitis.

WARNING

Selenium Injection can be toxic if given in excessive amounts. Supplementation of TPN solution with selenium should be immediately discontinued if toxicity symptoms are observed. Frequent determination of plasma selenium levels during TPN support and close medical supervision is recommended.

Selenium Injection is a hypotonic solution and should be administered in admixtures only.

This product contains aluminum that may be toxic. Aluminum may reach toxic levels with prolonged parenteral administration if kidney function is impaired. Premature neonates are particularly at risk because their kidneys are immature, and they require large amounts of calcium and phosphate solutions, which contain aluminum.

Research indicates that patients with impaired kidney function, including premature neonates, who receive parenteral levels of aluminum at greater than 4 to 5 mcg/kg/day accumulate aluminum at levels associated with central nervous system and bone toxicity. Tissue loading may occur at even lower rates of administration.

PRECAUTIONS

As selenium is eliminated in urine and feces, selenium supplements may be adjusted, reduced or omitted in renal dysfunction and/or gastrointestinal malfunction. In patients receiving blood transfusions, contribution from such transfusions should also be considered. Frequent selenium plasma level determinations are suggested as a guideline.

In animals, selenium has been reported to enhance the action of Vitamin E and decrease the toxicity of mercury, cadmium and arsenic.

Pregnancy

Teratogenic Effects
Pregnancy Category C: Selenium at high dose levels (15-30 mcg/egg) has been reported to have adverse embryological effects among chickens. There are however, no adequate and well controlled studies in pregnant women. Selenium Injection should be used during pregnancy only if potential benefit justifies the potential risk to the fetus.

Presence of selenium in placenta and umbilical cord blood has been reported in humans.

ADVERSE REACTIONS

The amount of selenium present in Selenium Injection is small. Symptoms of toxicity from selenium are unlikely to occur at the recommended dosage level. To report SUSPECTED ADVERSE REACTIONS, contact Pangea Pharmaceuticals, LLC at 1-855-892-8224 or FDA at 1-800-FDA-1088 or www.fda.gov/medwatch

OVERDOSAGE

Chronic toxicity in humans resulting from exposure to selenium in industrial environments, intake of foods grown in seleniferous soils, use of selenium-contaminated water, and application of cosmetics containing selenium has been reported in literature. Toxicity symptoms include hair loss, weakened nails, dermatitis, dental defects, gastrointestinal disorders, nervousness, mental depression, metallic taste, vomiting, and garlic odor of breath and sweat. Acute poisoning due to ingestion of large amounts of selenium compounds has resulted in death with histopathological changes including fulminating peripheral vascular collapse, internal vascular congestion, diffusely hemorrhagic, congested and edematus lungs, brick-red color gastric mucosa. The death was preceded by coma.

No effective antidote to selenium poisoning in humans is known. Animal studies have shown casein and linseed oil in feeds, reduced glutathione, arsenic, magnesium sulfate, and bromobenzene to afford limited protection.

DOSAGE AND ADMINISTRATION

Selenium Injection provides 40 mcg selenium/mL. For metabolically stable adults receiving TPN, the suggested additive dosage level is 20 to 40 mcg selenium/day. For pediatric patients, the suggested additive dosage level is 3 mcg/kg/day.

In adults, selenium deficiency states resulting from long-term TPN support, selenium as selenomethionine or selenious acid, administered intravenously at 100 mcg/day for a period of 24 and 31 days, respectively, has been reported to reverse deficiency symptoms without toxicity.

Aseptic addition of Selenium Injection to parenteral nutrition solutions under laminar flow hood is recommended. Selenium is physically compatible with the electrolytes and other trace elements usually present in parenteral nutrition formulations. Frequent monitoring of plasma selenium levels is suggested as a guideline for subsequent administration. The normal whole blood range for selenium is approximately 10 to 37 mcg/100 mL.

Do not directly mix ascorbic acid injection with selenium containing parenteral products in the same syringe or vial, as this admixture may cause the formation of an insoluble precipitate.

Parenteral drug products should be inspected visually for particulate matter and discoloration prior to administration, whenever solution and container permit.

HOW SUPPLIED

Selenium Injection containing selenious acid 65.4 mcg/mL (equivalent to elemental selenium 40 mcg/mL).

HOW SUPPLIED | NDC NUMBER
Pharmacy Bulk Package 5 x 10 mL vials per carton | 81279-106-05
Pharmacy Bulk Package 10 mL Single-Use Vial | 81279-106-01

Store at 20° to 25°C (68° to 77°F); excursions permitted to 15° to 30°C (59° to 86°F) (See USP Controlled Room Temperature).

Manufactured for:Pangea Pharmaceuticals, LLC Brielle, NJ 08730

Rev. 04/2024

PRINICIPAL DISPLAY PANEL - Vial Labeling

NDC 81279-106-01
10 mL Single Use Vial
Rx Only
Selenious Acid Injection, USP
400 mcg*/10 mL
(40 mcg*/mL) of selenium
For intravenous use after dilution and admixing
PRESERVATIVE FREE.
10 mL
PHARMACY BULK PACKAGE

PRINICIPAL DISPLAY PANEL - Carton Labeling

NDC 81279-106-05

Rx Only
Selenious Acid Injection, USP
400 mcg*/10 mL
(40 mcg*/mL) of selenium
For intravenous use after dilution and admixing
STERILE
PRESERVATIVE FREE.
5x 10 mL VIALS
PHARMACY BULK PACKAGE